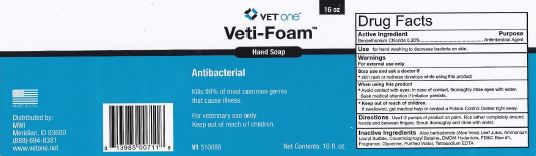 DRUG LABEL: Veti-Foam
NDC: 13985-529 | Form: LIQUID
Manufacturer: MWI/Vet One
Category: otc | Type: HUMAN OTC DRUG LABEL
Date: 20111228

ACTIVE INGREDIENTS: BENZETHONIUM CHLORIDE 2.0 g/1.0 L
INACTIVE INGREDIENTS: EDETATE SODIUM; GLYCERIN; WATER; AMMONIUM LAURYL SULFATE; COCAMIDOPROPYL BETAINE; ALOE VERA LEAF; DMDM HYDANTOIN; FD&C BLUE NO. 1

Veti-Foam Hand Soap

Active ingredient(s)

Benzethonium Chloride 0.20%

Use(s)

for hand washing to decrease bacteria on skin

Warnings

When using this product

- Avoid contact with eyes; in case of contact, thoroughly rinse eyes with water. Seek medical attention if irritation persists.

Stop use and ask a doctor if

- skin rash or redness develops when using this product

Keep out of reach of children

If swallowed, get medical help or contact a Poison Control Center right away.

Directions

Use 1-2 pumps of product on plam. Rub lather completely around hands and between fingers. Scrub thoroughly and rinse with water.

Inactive ingredients

Aloe barbadensis (Aloe Vera) Leaf Juice, Ammonium lauryl Sulfate, Cocamidoprpyl Betaine, DMDM Hydantoin, FD&C Blue #1, Fragrance, Glycerin, Purified Water, EDTA

Principal Display Panel

16oz label